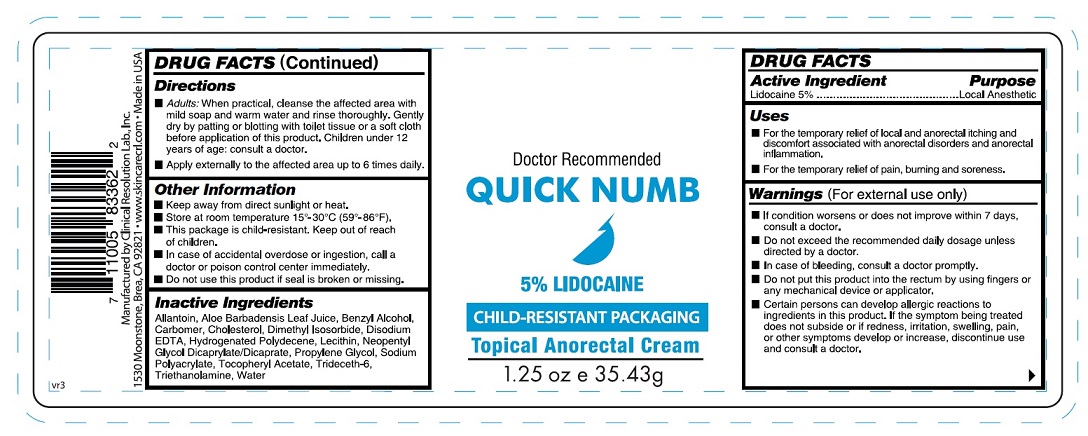 DRUG LABEL: Quick Numb
NDC: 63742-110 | Form: CREAM
Manufacturer: Clinical Resolution Laboratory, Inc.
Category: otc | Type: HUMAN OTC DRUG LABEL
Date: 20220708

ACTIVE INGREDIENTS: LIDOCAINE 50 mg/1 g
INACTIVE INGREDIENTS: ALLANTOIN; ALOE VERA LEAF; BENZYL ALCOHOL; CARBOMER INTERPOLYMER TYPE A (ALLYL SUCROSE CROSSLINKED); CHOLESTEROL; DIMETHYL ISOSORBIDE; EDETATE DISODIUM ANHYDROUS; HYDROGENATED POLYDECENE (1500 CST); EGG PHOSPHOLIPIDS; NEOPENTYL GLYCOL DICAPRYLATE/DICAPRATE; PROPYLENE GLYCOL; WATER; SODIUM POLYACRYLATE (8000 MW); .ALPHA.-TOCOPHEROL ACETATE; TRIDECETH-6; TROLAMINE

Active Ingredient

Lidocaine 5%

Purpose

Local Anesthetic

Uses:

- For the temporary relief of local and anorectal itching and discomfort associated with anorectal disorders and anorectal inflammation
- For the temporary relief of pain, burning and soreness.

Warnings

- If condition worsens or does not improve within 7 days, consult a doctor.
- Do not exceed the recommended daily dosage unless directed by a doctor.
- In case of bleeding, consult a doctor promptly.
- Do not put this product into the rectum by using fingers or any mechanical device or applicator.
- Certain persons can develop allergic reactions to ingredients in this product. If the symptom being treated does not subside or if redness, irritation, swelling, pain, or other symptoms develop or increase, discontinue use and consult a doctor.

Keep out of reach of children

In case of accidental ingestion, seek medical attention immediately.

Directions

- Adults: When practical, cleanse the affected area with mild soap and warm water and rinse thoroughly. Gently dry by patting or blotting with toilet tissue or a soft cloth before application of this product. Children under 12 years of age: consult a doctor.
- Apply externally to the affected area up to 6 times daily.

Other Information

- Keep away from direct sunlight or heat.
- Store at room temperature 15°-30°C (59°-86°F).
- This package is child-resistant. Keep out of reach of children.
- In case of accidental overdose or ingestion, call a doctor or poison control center immediately.
- Do not use this product if seal is broken or missing.

Inactive Ingredients

Allanloin, Aloe Barbadensis Leaf Juice, Benzyt Alcohol,Carbomer, Cholesterol, Dlmethyt lsosorbide, DisodiumEDTA, Hydrogenated Polydecene, Lecithin, NeopenlytGlycol Dicaprylale/Dicaprate. Propylene Glycol, Water,Sodium Polyacrytate, Tocopheryt Acetate, Trideceth-6,Triethanolamine